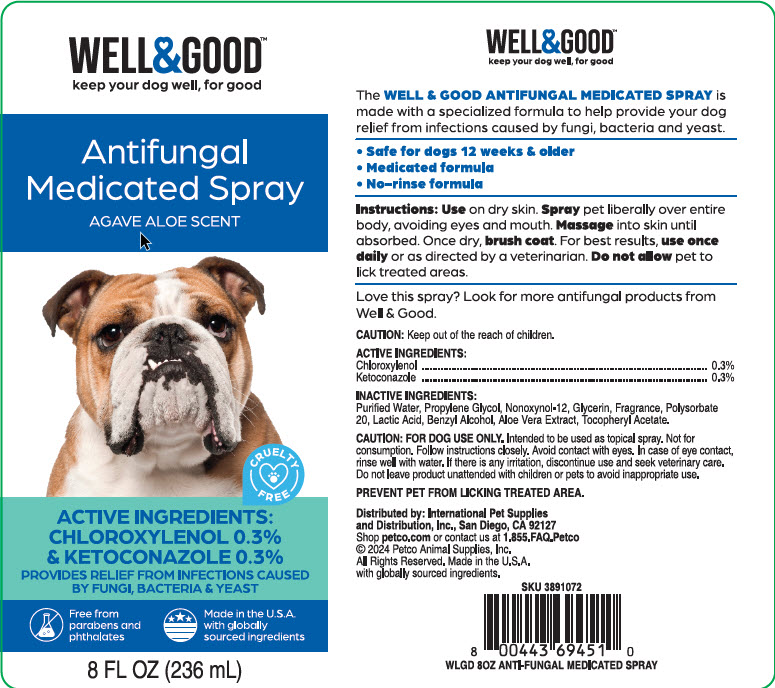 DRUG LABEL: Well and Good
NDC: 27102-521 | Form: SPRAY
Manufacturer: International Pet Supplies & Distribution
Category: animal | Type: OTC ANIMAL DRUG LABEL
Date: 20240913

ACTIVE INGREDIENTS: Chloroxylenol 3 mg/236 mL; KETOCONAZOLE 3 mg/236 mL

Antifungal Medicated Spray

Caution

FOR DOG USE ONLY. Intended to be used as topical spray. Not for consumption. Follow instructions closely. Avoid contact with eyes. In case of eye contact, rinse well with water. If there is any irritation, discontinue use and seek veterinary care. Do not leave product unattended with children or pets to avoid inappropriate use.

Prevent pet from licking treated area.

Instructions

Use on dry skin. Spray pet liberally over entire body, avoiding eyes and mouth. Massage into skin until absorbed. Once dry, brush coat. For best results, use once daily or as directed by a veterinarian. Do no allow pet to lick treated areas.